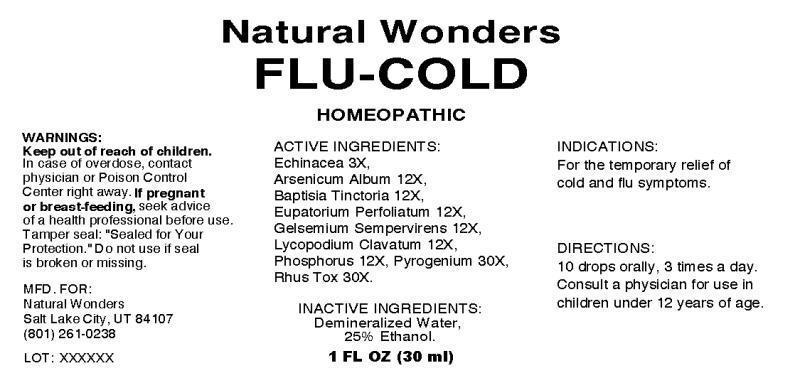 DRUG LABEL: Flu-Cold
NDC: 54146-0001 | Form: LIQUID
Manufacturer: Natural Wonders
Category: homeopathic | Type: HUMAN OTC DRUG LABEL
Date: 20200218

ACTIVE INGREDIENTS: ECHINACEA ANGUSTIFOLIA 3 [hp_X]/1 mL; ARSENIC TRIOXIDE 12 [hp_X]/1 mL; BAPTISIA TINCTORIA ROOT 12 [hp_X]/1 mL; EUPATORIUM PERFOLIATUM FLOWERING TOP 12 [hp_X]/1 mL; GELSEMIUM SEMPERVIRENS ROOT 12 [hp_X]/1 mL; LYCOPODIUM CLAVATUM SPORE 12 [hp_X]/1 mL; PHOSPHORUS 12 [hp_X]/1 mL; RANCID BEEF 30 [hp_X]/1 mL; TOXICODENDRON PUBESCENS LEAF 30 [hp_X]/1 mL
INACTIVE INGREDIENTS: WATER; ALCOHOL

Drug Facts

ACTIVE INGREDIENTS:

Echinacea (Angustifolia) 3X, Arsenicum Album 12X, Baptisia Tinctoria 12X, Eupatorium Perfoliatum 12X, Gelsemium Sempervirens 12X, Lycopodium Clavatum 12X, Phosphorus 12X, Pyrogenium 30X, Rhus Tox 30X.

INDICATIONS:

For the temporary relief of cold and flu symptoms.

WARNINGS:

Keep out of reach of children. In case of overdose, contact physician or Poison Control Center right away.

If pregnant or breast-feeding, seek advice of a health professional before use.

Tamper seal: "Sealed for Your Protection." Do not use if seal is broken or missing.

DIRECTIONS:

10 drops orally, 3 times a day. Consult a physician for use in children under 12 years of age.

INACTIVE INGREDIENTS:

Demineralized Water, 25% Ethanol

Keep out of reach of children. In case of overdose, contact physician or Poison Control Center right away.

INDICATIONS:

For the temporary relief of cold and flu symptoms.

QUESTIONS:

MFD. FOR:

Natural Wonders

Salt Lake City, UT 84107

(801) 261-0238

PACKAGE LABEL DISPLAY:

Natural Wonders

FLU-COLD

HOMEOPATHIC

1 FL OZ (30 ml)